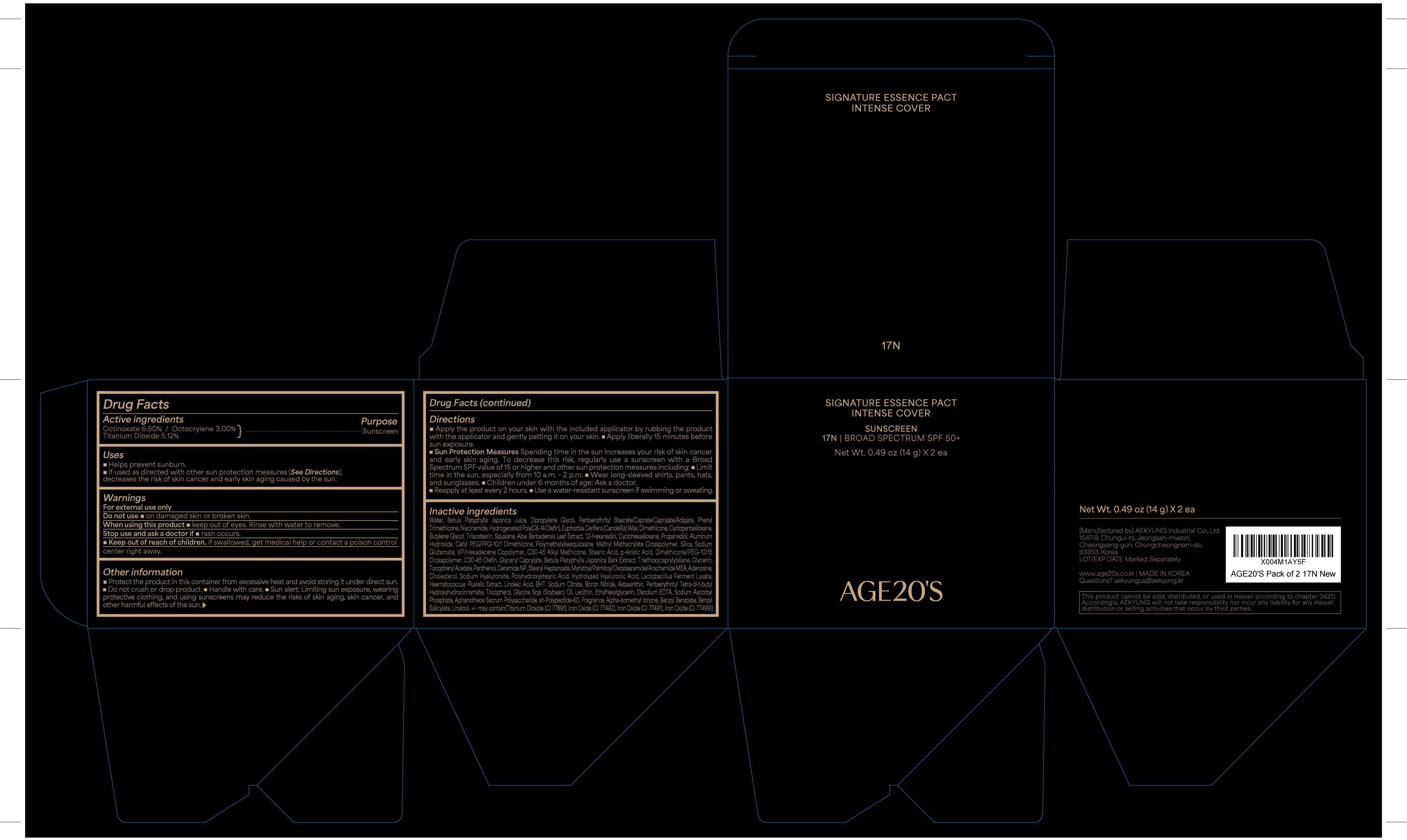 DRUG LABEL: AGE20S SIGNATURE ESSENCE PACT INTENSE COVER 17N PACK OF 2
NDC: 67225-5016 | Form: CREAM
Manufacturer: Aekyung Industrial Co., Ltd.
Category: otc | Type: HUMAN OTC DRUG LABEL
Date: 20251209

ACTIVE INGREDIENTS: TITANIUM DIOXIDE 0.7168 g/14 g; OCTINOXATE 0.91 g/14 g; OCTOCRYLENE 0.42 g/14 g
INACTIVE INGREDIENTS: CERAMIDE NP; ALUMINUM HYDROXIDE; CETYL PEG/PPG-10/1 DIMETHICONE (HLB 2); FERRIC OXIDE RED; SOYBEAN OIL; PANTHENOL; GLYCERIN; FERROSOFERRIC OXIDE; GLYCERYL CAPRYLATE; BORON NITRIDE; HAEMATOCOCCUS PLUVIALIS; DIPROPYLENE GLYCOL; STEARYL HEPTANOATE; WATER; DIMETHICONE; BETULA PLATYPHYLLA BARK; BETULA PLATYPHYLLA VAR. JAPONICA RESIN; LINOLEIC ACID; POLYMETHYLSILSESQUIOXANE (11 MICRONS); POLYHYDROXYSTEARIC ACID STEARATE; HYDROGENATED SOYBEAN LECITHIN; BUTYLENE GLYCOL; C30-45 OLEFIN; C30-45 ALKYL METHICONE; CYCLOMETHICONE 6; MONOSODIUM GLUTAMATE; PHENYL TRIMETHICONE; ALPHA-TOCOPHEROL ACETATE; CHOLESTEROL; HYALURONIC ACID; MYRISTOYL/PALMITOYL OXOSTEARAMIDE/ARACHAMIDE MEA; ALOE VERA LEAF; HYDROGENATED POLY(C6-14 OLEFIN; 2 CST); ASTAXANTHIN; ADENOSINE; VINYLPYRROLIDONE/HEXADECENE COPOLYMER; TRIETHOXYCAPRYLYLSILANE; CYCLOMETHICONE 5; ETHYLHEXYLGLYCERIN; FERRIC OXIDE YELLOW; STEARIC ACID; HYALURONATE SODIUM; SQUALANE; 1,2-HEXANEDIOL; CANDELILLA WAX; ALUMINUM OXIDE; DIETHYLAMINO HYDROXYBENZOYL HEXYL BENZOATE; PROPANEDIOL; TRIISOSTEARIN; NIACINAMIDE; P-ANISIC ACID

67225-5016 AGE20S SIGNATURE ESSENCE PACT INTENSE COVER 17N PACK OF 2

ACTIVE INGREDIENT

Octinoxate 6.50%

Octocrylene 3.00%

Titanium Dioxide 5.12%

PURPOSE

Sunscreen

INDICATIONS AND USAGE

■ Helps prevent sunburn.

■ If used as directed with other sun protection measures (see Directions), decreases the risk of skin cancer and early skin aging caused by the sun.

WARNINGS

For external use only.

Do not use on damaged skin or broken skin.

When using this product keep out of eyes. Rinse with water to remove.

Stop use and ask a doctor if rash occurs.

Keep out of reach of children. If swallowed, get medical help or contact a Poison control center right away.

OTHER SAFETY INFORMATION

Protect the product in this container from excessive heat and avoid storing it under direct sun. ■ Do not crush or drop product. ■ Handle with care. ■ Sun alert: Limiting sun exposure, wearing protective clothing, and using sunscreens may reduce the risks of skin aging, skin cancer, and other harmful effects of the sun.

Directions
Apply the product on your skin with the included applicator by rubbing the product with the applicator and gently patting it on your skin. Apply liberally 15 minutes before sun exposure.
■ Sun Protection Measures. Spending time in the sun increases your risk of skin cancer and early skin aging. To decrease this risk, regularly use a sunscreen with a Broad Spectrum SPF value of 15 or higher and other sun protection measures including:■ Limit time in the sun, especially from 10 a.m. - 2 p.m. Wear long-sleeved shirts, pants, hats, and sunglasses. Children under 6 months of age: Ask a doctor.
■Reapply at least every 2 hours. Use a water-resistant sunscreen if swimming or sweating.

INACTIVE INGREDIENT

Water, Betula Platyphylla Japonica Juice, Dipropylene Glycol, Pentaerythrityl Stearate/Caprate/Caprylate/Adipate, Phenyl Trimethicone, Niacinamide, Hydrogenated Poly(C6-14 Olefin), Euphorbia Cerifera (Candelilla) Wax, Dimethicone, Cyclopentasiloxane, Butylene Glycol, Triisostearin, Squalane, Aloe Barbadensis Leaf Extract, 1,2-Hexanediol, Cyclohexasiloxane, Propanediol, Aluminum Hydroxide, Cetyl PEG/PPG-10/1 Dimethicone, Polymethylsilsesquioxane, Methyl Methacrylate Crosspolymer, Silica, Sodium Glutamate, VP/Hexadecene Copolymer, C30-45 Alkyl Methicone, Stearic Acid, p-Anisic Acid, Dimethicone/PEG-10/15 Crosspolymer, C30-45 Olefin, Glyceryl Caprylate, Betula Platyphylla Japonica Bark Extract, Triethoxycaprylylsilane, Glycerin, Tocopheryl Acetate, Panthenol, Ceramide NP, Stearyl Heptanoate, Myristoyl/Palmitoyl Oxostearamide/Arachamide MEA, Adenosine, Cholesterol, Sodium Hyaluronate, Polyhydroxystearic Acid, Hydrolyzed Hyaluronic Acid, Lactobacillus Ferment Lysate, Haematococcus Pluvialis Extract, Linoleic Acid, BHT, Sodium Citrate, Boron Nitride, Astaxanthin, Pentaerythrityl Tetra-di-t-butyl Hydroxyhydrocinnamate, Tocopherol, Glycine Soja (Soybean) Oil, Lecithin, Ethylhexylglycerin, Disodium EDTA, Sodium Ascorbyl Phosphate, Aphanothece Sacrum Polysaccharide, sh-Polypeptide-60, Fragrance, Alpha-Isomethyl Ionone, Benzyl Benzoate, Benzyl Salicylate, Linalool, +/- may contain(Titanium Dioxide (CI 77891), Iron Oxide (CI 77492), Iron Oxide (CI 77491), Iron Oxide (CI 77499))